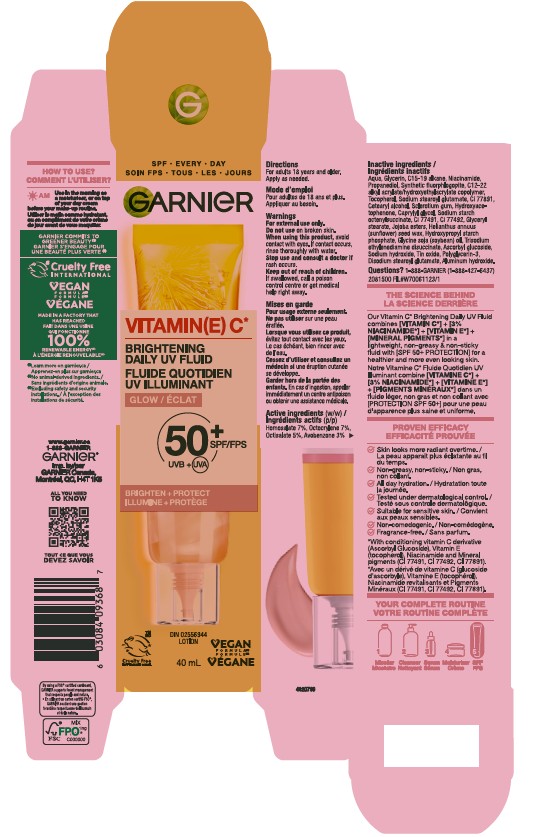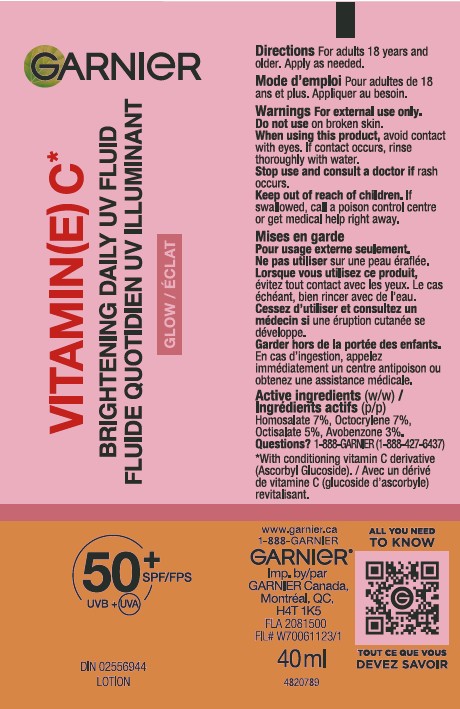 DRUG LABEL: Garnier Vitamin(E) C Brightening Daily UV Fluid Glow SPF 50 Plus UVB Plus UVA
NDC: 82046-687 | Form: CREAM
Manufacturer: L’Oreal USA Products Inc
Category: otc | Type: HUMAN OTC DRUG LABEL
Date: 20251209

ACTIVE INGREDIENTS: OCTOCRYLENE 70 mg/1 mL; HOMOSALATE 70 mg/1 mL; OCTISALATE 50 mg/1 mL; AVOBENZONE 30 mg/1 mL
INACTIVE INGREDIENTS: AQUA; GLYCERIN; C15-19 ALKANE; NIACINAMIDE; PROPANEDIOL; MAGNESIUM POTASSIUM ALUMINOSILICATE FLUORIDE; TOCOPHEROL; SODIUM STEAROYL GLUTAMATE; TITANIUM DIOXIDE; CETEARYL ALCOHOL; SCLEROTIUM GUM; HYDROXYACETOPHENONE; CAPRYLYL GLYCOL; FERRIC OXIDE RED; FERRIC OXIDE YELLOW; GLYCERYL STEARATE; JOJOBA OIL; SUNFLOWER SEED; SOYBEAN OIL; TRISODIUM ETHYLENEDIAMINE DISUCCINATE; ASCORBYL GLUCOSIDE; SODIUM HYDROXIDE; TIN OXIDE; POLYGLYCERIN-3; DISODIUM STEAROYL GLUTAMATE; ALUMINUM HYDROXIDE

Drug Facts

Directions

For adults 18 years and older. Apply as needed.

Warnings

For external use only.

Do not use

on broken skin.

When using

this product, avoid contact with eyes. If contact occurs, rinse thoroughly with water.

Stop use

and consult a doctor if rash occurs.

Keep out of reach of children.

If swallowed, call a poison control centre or get medical help right away.

Active ingredients (w/w)

Homosalate 7%, Octocrylene 7%, Octisalate 5%, Avobenzone 3%

Inactive ingredients

Aqua, Glycerin, C15-19 alkane, Niacinamide, Propanediol, Synthetic fluorphlogopite, C12-22 alkyl acrylate/hydroxyethylacrylate copolymer, Tocopherol, Sodium stearoyl glutamate, Ci 77891, Cetearyl alcohol, Sclerotium gum, Hydroxyacetophenone, Caprylyl glycol, Sodium starch octenylsuccinate, Ci 77491, Ci 77492, Glyceryl stearate, Jojoba esters, Helianthus annuus (sunflower) seed wax, Hydroxypropyl starch phosphate, Glycine soja (soybean) oil, Trisodium ethylenediamine disuccinate, Ascorbyl glucoside, Sodium hydroxide, Tin oxide, Polyglycerin-3, Disodium stearoyl glutamate, Aluminum hydroxide

Questions?

1-888-GARNIER (1-888-427-6437)